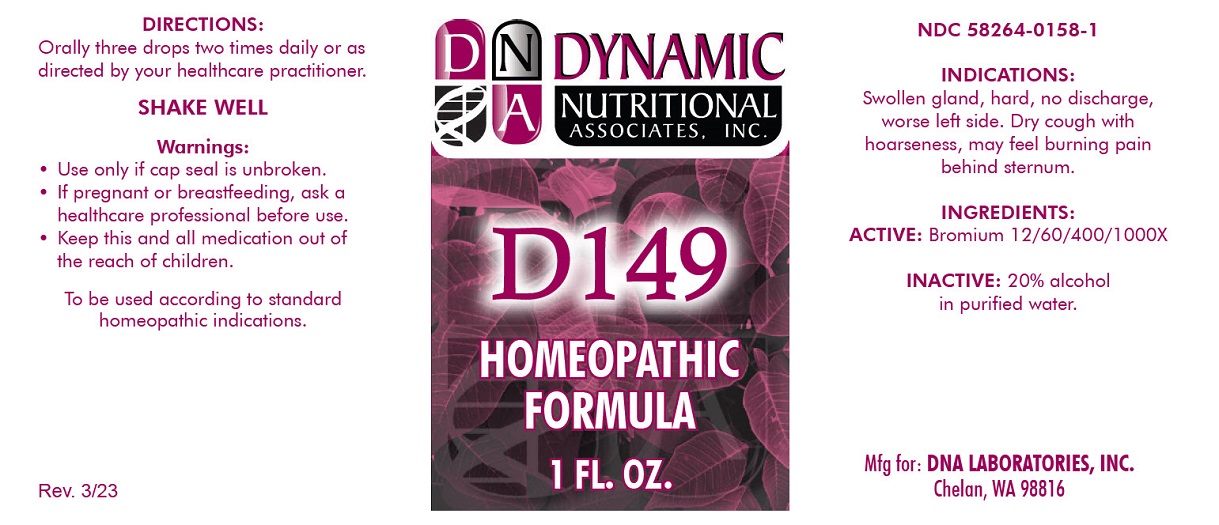 DRUG LABEL: D-149
NDC: 58264-0158 | Form: SOLUTION
Manufacturer: DNA Labs
Category: homeopathic | Type: HUMAN OTC DRUG LABEL
Date: 20250113

ACTIVE INGREDIENTS: BROMINE 1000 [hp_X]/1 mL
INACTIVE INGREDIENTS: ALCOHOL; WATER

D-149

NDC 58264-0158-1

INDICATIONS AND USAGE

PURPOSE

Swollen glands, hard, no discharge, worse left side.

Dry cough with hoarseness, may feel burning pain behind sternum.

INGREDIENTS

ACTIVE

Bromine 12/60/400/1000X

INACTIVE

20% alcohol in purified water.

SUGGESTED DOSAGE

Orally three drops two times daily or as directed by your healthcare practitioner.

STORAGE AND HANDLING

SHAKE WELL

WARNINGS

- Use only if cap seal is unbroken.

PREGNANCY OR BREAST FEEDING

- If pregnant or breastfeeding, ask a healthcare professional before use.

KEEP OUT OF REACH OF CHILDREN

- Keep this and all medication out of the reach of children.

To be used according to standard homeopathic indications.

PRINCIPAL DISPLAY PANEL - 1 FL. OZ. - Bottle Label

DYNAMIC

NUTRITIONAL

ASSOCIATES, INC.

D-149

HOMEOPATHIC

1 FL. OZ.